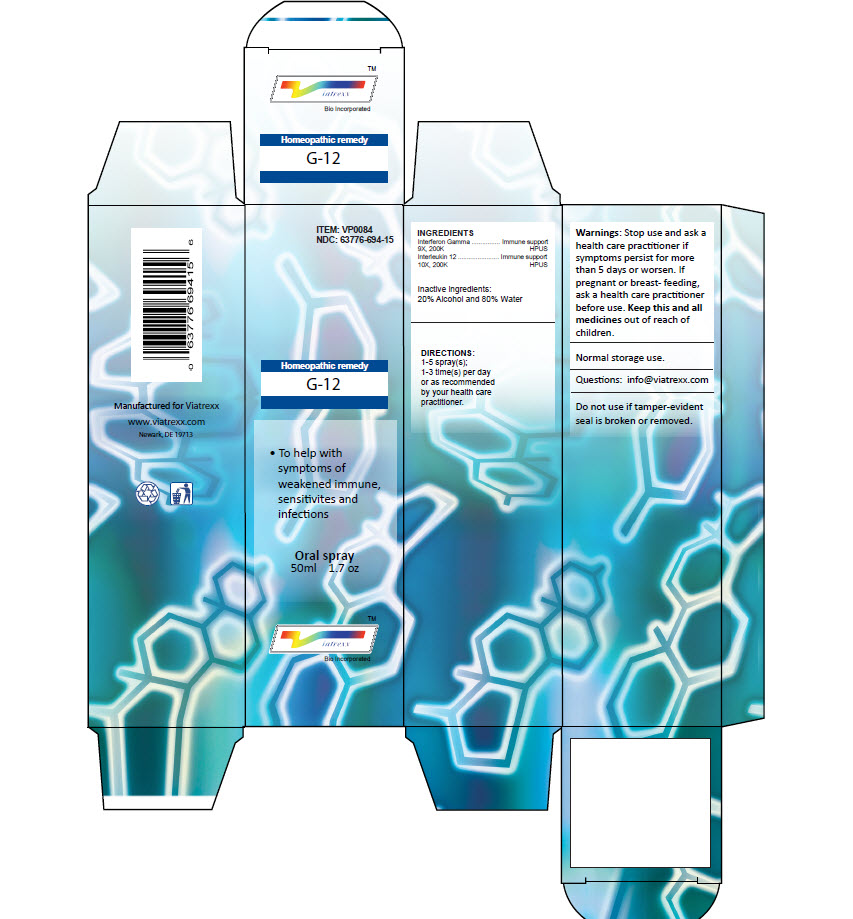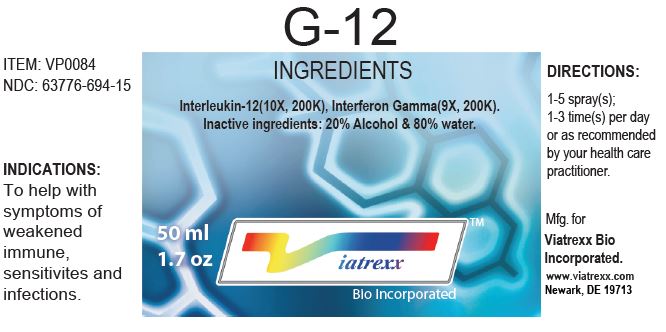 DRUG LABEL: G-12
NDC: 63776-694 | Form: SPRAY
Manufacturer: VIATREXX BIO INCORPORATED
Category: homeopathic | Type: HUMAN OTC DRUG LABEL
Date: 20221130

ACTIVE INGREDIENTS: INTERLEUKIN-12 HUMAN 200 [kp_C]/1 mL; INTERFERON GAMMA-1A 200 [kp_C]/1 mL
INACTIVE INGREDIENTS: ALCOHOL; WATER

G-12

Active Ingredients

Interleukin 12 (10X, 200K), Interferon Gamma (9X, 200K)

Purpose:

Interleukin 12 | Immune support
Interferon Gamma | Immune support

Uses

To help with symptoms of weakened immune, sensitivites and infections.

Warnings

Stop use and ask a health care practitioner if symptoms persist for more than five days or worsen. If pregnant or breastfeeding, ask a health care practitioner before use.

Dosage

1-5 spray(s); 1-3 time(s) per day or as recommended by your health care practitioner.

KEEP OUT OF REACH OF CHILDREN

Keep this and all medicines out of reach of children.

Other Ingredients

20% Alcohol and 80% Water

Other Information

Normal storage use.
Do not use if tamper-evident seal is broken or removed.

Questions

info@viatrexx.com

Principal Display Panel

ITEM: VP0084
NDC 63776-694-15
Homeopathic remedy
G-12
• To help with symptoms of weakened immune, sensitivites and infections.
Oral spray
50ml 1.7 oz
Viatrexx™ Bio Incorporated
Manufactured by Viatrexx
www.viatrexx.com
Newark, DE 19713

G-12
50 ml
1.7 oz
Viatrexx™ Bio Incorporated
ITEM: VP0084
NDC: 63776-694-15
INDICATIONS:
To help with symptoms of weakened immune, sensitivites and infections.
DIRECTIONS:
1-5 spray(s); 1-3 time(s) per day or as recommended by your health care practitioner.
Mfg. for
Viatrexx Bio Incorporated.
www.viatrexx.com
Newark, DE 19713